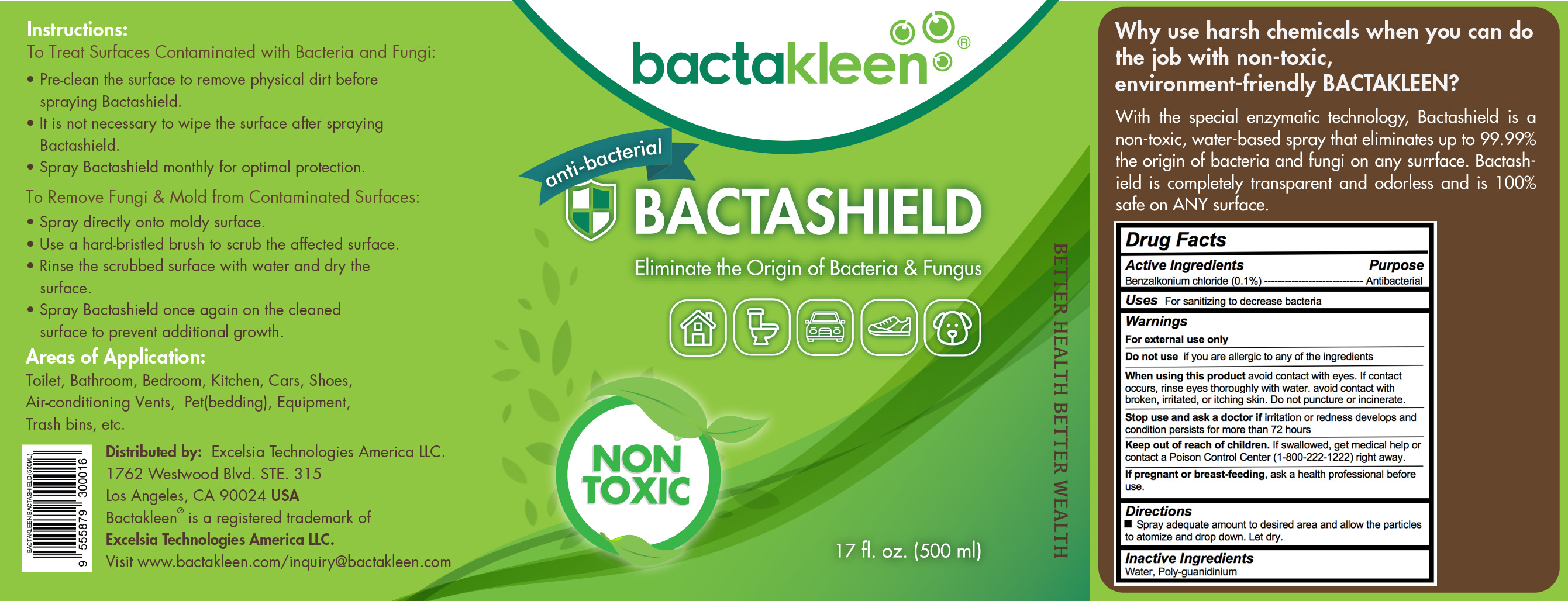 DRUG LABEL: Bactakleen Bactashield (500ml)
NDC: 73215-106 | Form: LIQUID
Manufacturer: Excelsia Technologies Sdn Bhd
Category: otc | Type: HUMAN OTC DRUG LABEL
Date: 20200317

ACTIVE INGREDIENTS: BENZALKONIUM CHLORIDE 0.5 g/500 mL
INACTIVE INGREDIENTS: WATER

Bactakleen Bactashield (500ml)

Active Ingredients

Benzalkonium chloride (0.1%)

Purpose

Antibacterial

Keep out of reach of children

If swallowed, get medical help or contact a Poison Control Center (1-800-222-1222) right away.

Uses

For sanitizing to decrease bacteria

Warnings

For external use only

Do not use if you are allergic to any of the ingredients

When using this product avoid contact with eyes. If contact occurs, rinse eyes thoroughly with water. avoid contact with broken, irritated, or itching skin. Do not puncture or incinerate.

Stop use and ask a doctor if irritation or redness develops and condition persists for more than 72 hours

If pregnant or breast-feeding, ask a health professional before use.

Directions

Spray adequate amount to desired area.

Inactive Ingredients

Water, Poly-guanidinium